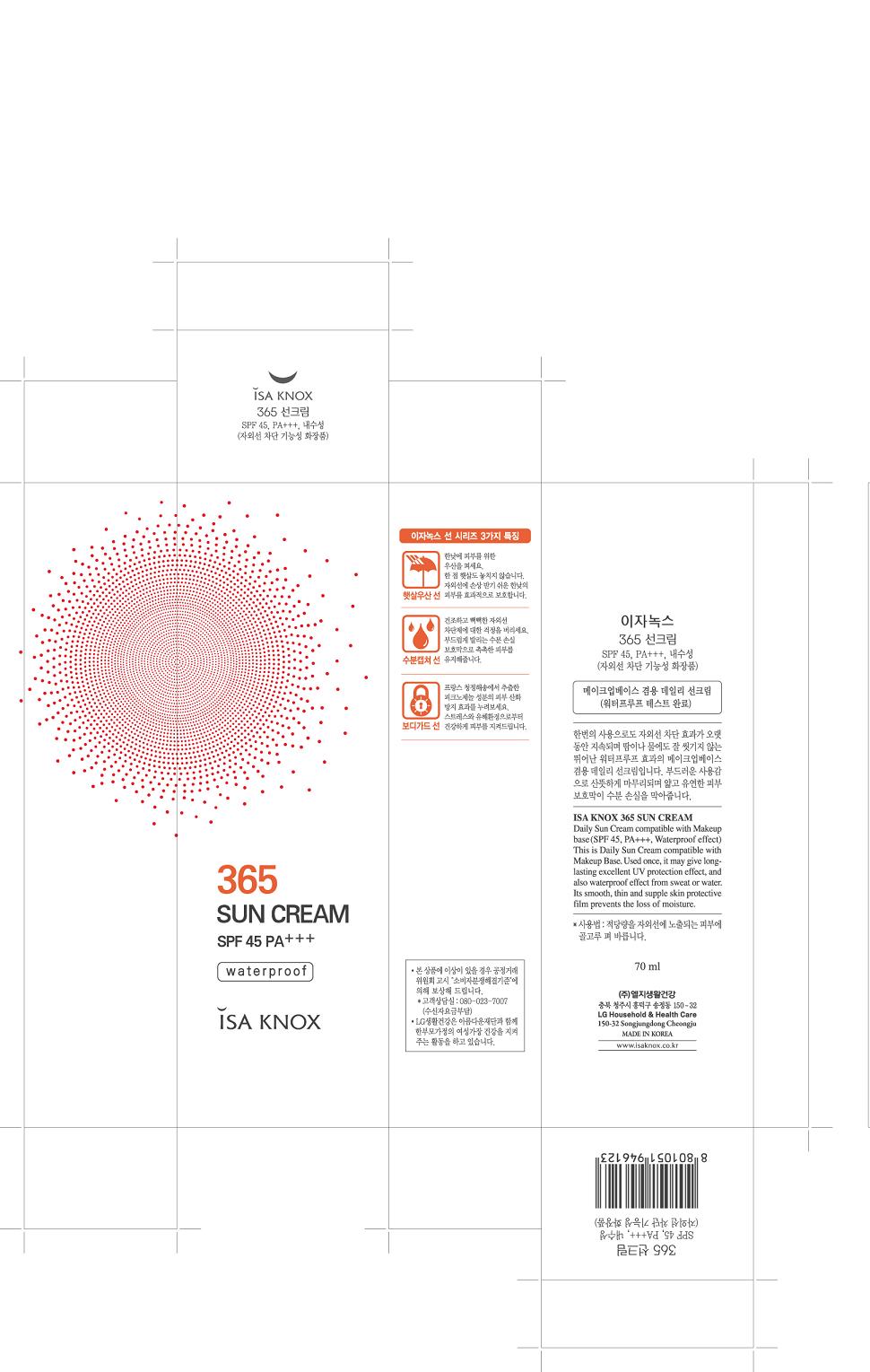 DRUG LABEL: ISA KNOX 365 SUN
NDC: 53208-502 | Form: CREAM
Manufacturer: LG Household and Healthcare, Inc.
Category: otc | Type: HUMAN OTC DRUG LABEL
Date: 20110310

ACTIVE INGREDIENTS: ZINC OXIDE 11.04 mL/100 mL; OCTINOXATE 7.2 mL/100 mL; TITANIUM DIOXIDE 4.03 mL/100 mL
INACTIVE INGREDIENTS: WATER; ZINC OXIDE; BUTYLENE GLYCOL; CYCLOMETHICONE 5 ; DIPROPYLENE GLYCOL; DIMETHICONE; MAGNESIUM SULFATE, UNSPECIFIED; SORBITAN SESQUIOLEATE; PANTHENOL; METHYLPARABEN; CHAMAEMELUM NOBILE FLOWER; ETHYLPARABEN; SACCHARIDE ISOMERATE; ACETATE ION; DISTEARYLDIMONIUM CHLORIDE; ZINC STEARATE; CETYL ETHYLHEXANOATE; FRUIT; MARITIME PINE

Drug Facts

ACTIVE INGREDIENT

ZINC OXIDE 11.04%

OCTINOXATE 7.02%

TITANIUM DIOXIDE 4.03%

WARNINGS AND PRECAUTIONS

For external use only

Keep out of reach of children. Is swallowed, get medical help or contact a Poison Control Center right away.

WHEN USING

Keep out of eyes. Rinse with water to remove.

Stop use if a rash or irritation develops and lasts.

PACKAGE LABEL

Isaknox
365 Sun Cream